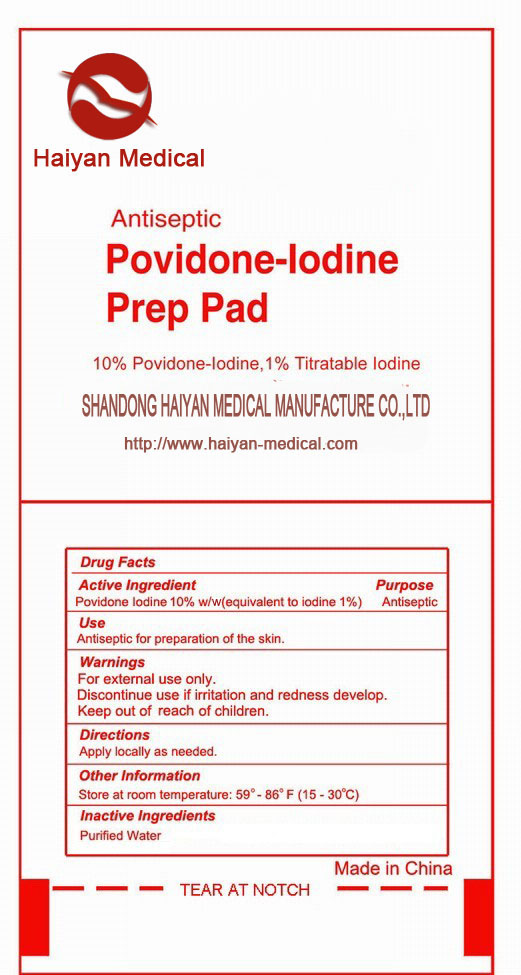 DRUG LABEL: Povidone-Iodine Pad
NDC: 42339-003 | Form: SWAB
Manufacturer: Shandong Haiyan Medical Manufacture Co., Ltd.
Category: otc | Type: HUMAN OTC DRUG LABEL
Date: 20220319

ACTIVE INGREDIENTS: POVIDONE-IODINE 9.43 g/100 g
INACTIVE INGREDIENTS: CITRIC ACID MONOHYDRATE; SODIUM PHOSPHATE; WATER

42339-003 Antiseptic Povidone-Iodine Prep Pad 10% Povidone-Iodine, 1% available Iodine. SHANDONG HAIYAN MEDICAL MANUFACTURE CO., LTD. www. haiyan-medical.com

Active Ingredient

Povidone Iodine 10% w/w (equivalent to iodine 1%)

Purpose

Antiseptic

Use

Antiseptic for preparation of the skin.

Warnings

For external use only.
Discontinue use if irritation and redness develop.

Keep out of reach of Children.

Directions

Apply locally as needed.
Other Information
Store at room temperature: 59°- 86°F(15 - 30℃)

Inactive ingredients

Purified Water